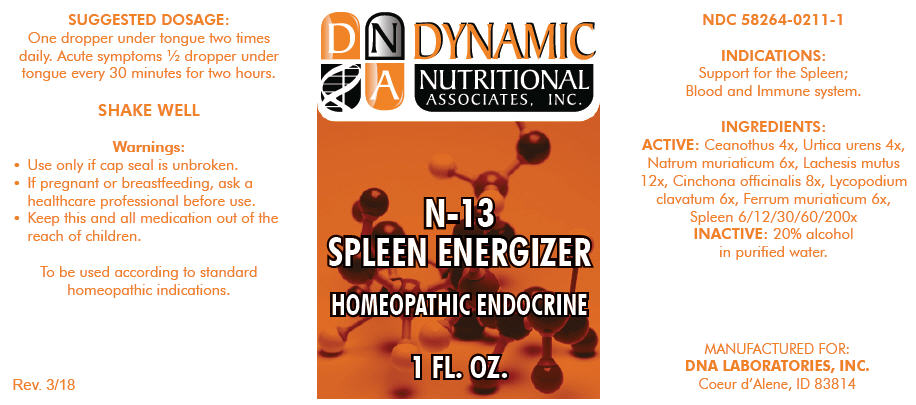 DRUG LABEL: N-13
NDC: 58264-0211 | Form: SOLUTION
Manufacturer: DNA Labs, Inc.
Category: homeopathic | Type: HUMAN OTC DRUG LABEL
Date: 20250109

ACTIVE INGREDIENTS: CEANOTHUS AMERICANUS LEAF 4 [hp_X]/1 mL; URTICA URENS 4 [hp_X]/1 mL; SODIUM CHLORIDE 6 [hp_X]/1 mL; LACHESIS MUTA WHOLE 12 [hp_X]/1 mL; CINCHONA OFFICINALIS BARK 8 [hp_X]/1 mL; LYCOPODIUM CLAVATUM WHOLE 6 [hp_X]/1 mL; FERRIC CHLORIDE HEXAHYDRATE 6 [hp_X]/1 mL; SUS SCROFA SPLEEN 200 [hp_X]/1 mL
INACTIVE INGREDIENTS: ALCOHOL; WATER

N-13

NDC 58264-0211-1

INDICATIONS

PURPOSE

Support for the Spleen; Blood and Immune system.

INGREDIENTS

ACTIVE

Ceanothus 4x, Urtica urens 4x, Natrum muriaticum 6x, Lachesis mutus 12x, Cinchona officinalis 8x, Lycopodium clavatum 6x, Ferrum muriaticum 6x, Spleen 6/12/30/60/200x

INACTIVE

20% alcohol in purified water.

SUGGESTED DOSAGE

One dropper under tongue two times daily. Acute symptoms ½ dropper under tongue every 30 minutes for two hours.

STORAGE AND HANDLING

SHAKE WELL

Warnings

- Use only if cap seal is unbroken.

PREGNANCY OR BREAST FEEDING

- If pregnant or breastfeeding, ask a healthcare professional before use.

KEEP OUT OF REACH OF CHILDREN

- Keep this and all medication out of the reach of children.

To be used according to standard homeopathic indications.

PRINCIPAL DISPLAY PANEL - 1 FL. OZ. Bottle Label

DYNAMIC
NUTRITIONAL
ASSOCIATES, INC.

N-13
SPLEEN ENERGIZER

HOMEOPATHIC ENDOCRINE

1 FL. OZ.